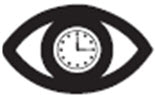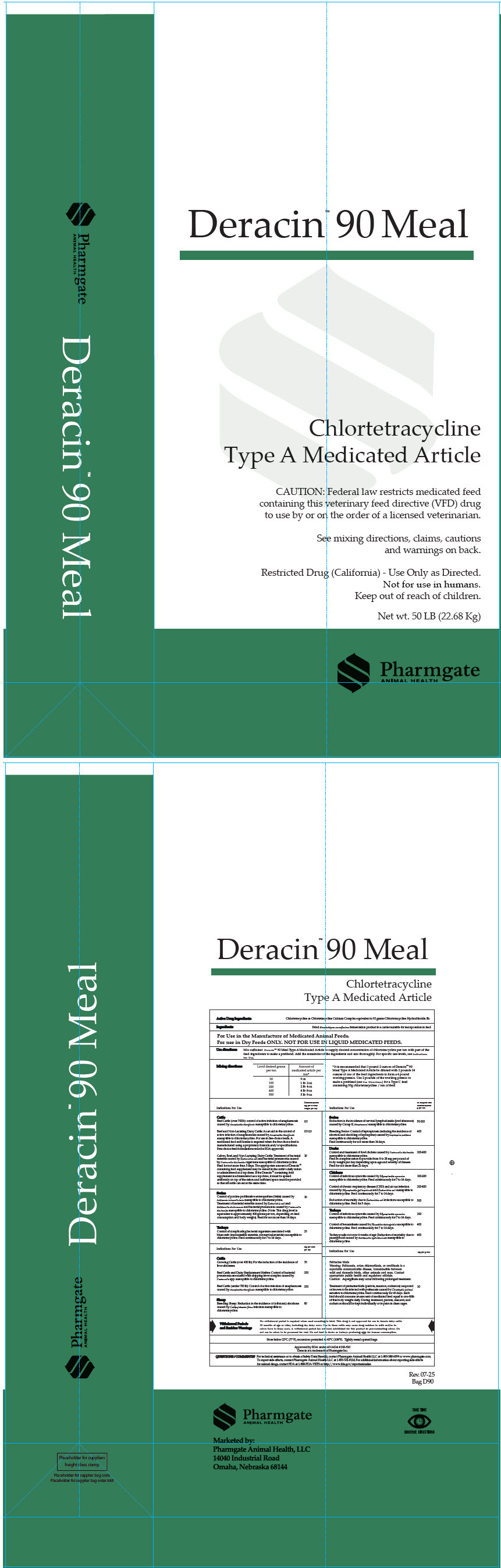 DRUG LABEL: Deracin 90 Meal
NDC: 51429-092 | Form: GRANULE
Manufacturer: Pharmgate Animal Health
Category: animal | Type: VFD TYPE A MEDICATED ARTICLE ANIMAL DRUG LABEL
Date: 20251009

ACTIVE INGREDIENTS: Chlortetracycline Calcium 198 g/1 kg

Deracin™ 90 Meal

Chlortetracyline

Type A Medicated Article

DESCRIPTION

Active Drug Ingredients: Chlortetracycline as Chlortetracycline Calcium Complex equivalent to 90 grams Chlortetracycline Hydrochloride/lb.

Ingredients: Dried Streptomyces aureofaciens fermentation product in a carrier suitable for incorporation in feed.

For Use in the Manufacture of Medicated Animal Feeds.

CAUTION: For use in Dry Feeds ONLY. NOT FOR USE IN LIQUID MEDICATED FEEDS.

VETERINARY INDICATIONS

Use directions: | Mix sufficient Deracin™ 90 Meal Type A Medicated Article to supply desired concentration of chlortetracycline per ton with part of the feed ingredients to make a preblend. Add the remainder of the ingredients and mix thoroughly. For specific use levels, see Indications for Use.
Mixing directions:
 | Level desired grams per ton | Amount of medicated article per ton [It is recommended that 1 pound 2 ounces of Deracin™ 90 Meal Type A Medicated Article be diluted with 2 pounds 14 ounces of one of the feed ingredients to form a 4 pound working premix. Use 2 pounds of the working premix to make a preblend (see Use Directions) for a Type C feed containing 50g chlortetracycline/ton of feed.]
 | 50 | 9 oz
 | 100 | 1lb 2 oz
 | 200 | 2 lb 4 oz
 | 400 | 4 lb 8 oz
 | 500 | 5 lb 9 oz
Indications for Use |  |  | Chlortetracycline mg per lb body weight per day
Cattle
Beef Cattle (over 700 lbs.): control of active infection of anaplasmosis caused by Anaplasma marginale susceptible to chlortetracycline. |  |  | 0.5
Beef and Non-Lactating Dairy Cattle: As an aid in the control of active infection of anaplasmosis caused by Anaplasma marginale susceptible to chlortetracycline. For use in free-choice feeds. A medicated feed mill license is required when the free-choice feed is manufactured using a proprietary formula and/or specifications. Free-choice feed formulations must be FDA approved. |  |  | 0.5-2.0
Calves, Beef, and Nonlactating Dairy Cattle: Treatment of bacterial enteritis caused by Escherichia coli and bacterial pneumonia caused by Pasteurella multocida organisms susceptible to chlortetracycline. Feed for not more than 5 days. The appropriate amount of Deracin ™ containing feed supplement may be mixed in the cattle's daily ration or administered as a top dress. If the Deracin ™ containing feed supplement is administered as a top dress, it must be spread uniformly on top of the ration and sufficient space must be provided so that all cattle can eat at the same time. |  |  | 10
Swine
Control of porcine proliferative enteropathies (ileitis) caused by Lawsonia intracellularis susceptible to chlortetracycline. Treatment of bacterial enteritis caused by Escherichia coli and Salmonella choleraesuis and bacterial pneumonia caused by Pasteurella multocida susceptible to chlortetracycline. (Note: This drug level is equivalent to approximately 400 grams per ton, depending on feed consumption and body weight). Feed for not more than 14 days. |  |  | 10
Turkeys
Control of complicating bacterial organisms associated with bluecomb (transmissible enteritis, coronaviral enteritis) susceptible to chlortetracycline. Feed continuously for 7 to 14 days. |  |  | 25
INDICATIONS FOR USE |  |  | mg per head per day
Cattle
Growing Cattle (over 400 lb.): For the reduction of the incidence of liver abscesses. |  |  | 70
Beef Cattle and Dairy Replacement Heifers: Control of bacterial pneumonia associated with shipping fever complex caused by Pasteurella spp. susceptible to chlortetracycline |  |  | 350
Beef cattle (under 700 lb.): Control of active infection of anaplasmosis caused by Anaplasma marginale susceptible to chlortetracycline. |  |  | 350
Sheep
Breeding Sheep: Reduction in the incidence of (vibrionic) abortions caused by Campylobacter fetus infection susceptible to chlortetracycline. |  |  | 80
Indications for Use |  |  | In complete feed chlortetracycline g per ton
Swine
Reduction in the incidence of cervical lymphadenitis (jowl abscesses) caused by Group E. Streptococci susceptible to chlortetracycline |  |  | 50-100
Breeding Swine: Control of leptospirosis (reducing the incidence of abortion and shedding of leptospirae) caused by Leptospira pomona susceptible to chlortetracycline. Feed continuously for not more than 14 days. |  |  | 400
Ducks
Control and treatment of fowl cholera caused by Pasteurella multocida susceptible to chlortetracycline. Feed in complete ration to provide from 8 to 28 mg per pound of body weight per day depending upon age and severity of disease. Feed for not more than 21 days. |  |  | 200-400
Chickens
Control of infectious synovitis caused by Mycoplasma synoviae susceptible to chlortetracycline. Feed continuously for 7 to 14 days. |  |  | 100-200
Control of chronic respiratory disease (CRD) and air sac infection caused by Mycoplasma gallisepticum and Escherichia coli susceptible to chlortetracycline. Feed continuously for 7 to 14 days. |  |  | 200-400
Reduction of mortality due to Escherichia coli infections susceptible to chlortetracycline. Feed for 5 days. |  |  | 500
Turkeys
Control of infectious synovitis caused by Mycoplasma synoviae susceptible to chlortetracycline. Feed continuously for 7 to 14 days. |  |  | 200
Control of hexamitiasis caused by Hexamita meleagrides susceptible to chlortetracycline. Feed continuously for 7 to 14 days. |  |  | 400
Turkey poults not over 4 weeks of age: Reduction of mortality due to paratyphoid caused by Salmonella typhimurium susceptible to chlortetracycline. |  |  | 400
Indications for Use |  |  | mg per g feed
Psittacine birds
Warning: Psittacosis, avian chlamydiosis, or ornithosis is a reportable communicable disease, transmissible between wild and domestic birds, other animals and man. Contact appropriate public health and regulatory officials.
Caution: Aspergillosis may occur following prolonged treatment.
Treatment of psittacine birds (parrots, macaws, cockatoos) suspected or known to be infected with psittacosis caused by Chlamydia psittaci sensitive to chlortetracycline. Feed continuously for 45 days. Each bird should consume an amount of medicated feed equal to one-fifth of this body weight daily. During treatment, parrots, macaws, and cockatoos should be kept individually or in pairs in clean cages. |  |  | 10

WARNINGS

Withdrawal Periods and Residue Warning:

No withdrawal period is required when used according to label. This drug is not approved for use in female dairy cattle 20 months of age or older, including dry dairy cows. Use in these cattle may cause drug residues in milk and/or in calves born to these cows. A withdrawal period has not been established for this product in pre-ruminating calves.
Do not use In calves to be processed for veal.
Do not feed to ducks or turkeys producing eggs for human consumption.

STORAGE AND HANDLING

Store below 25°C (77°F), excursions permitted to 40°C (104°F). Tightly reseal opened bags.

Approved by FDA under ANADA # 200-510
Deracin is a trademark of Pharmgate Inc.

QUESTIONS/COMMENTS?

For technical assistance or to obtain a Safety Data Sheet(s), contact Pharmgate Animal Health LLC at 1-800-380-6099 or www.pharmgate.com. To report side effects, contact Pharmgate Animal Health LLC at 1-833-531-0114. For additional information about reporting side effects for animal drugs, contact FDA at 1-888-FDA-VETS or http://www.fda.gov/reportanimalae

Marketed by:
Pharmgate Animal Health, LLC
14040 Industrial Road
Omaha, NE 68144

Take Time |  | Observe Directions | Rev. 07-25
 |  |  | Bag D90

PRINCIPAL DISPLAY PANEL - 22.68 Kg Bag Label

Deracin™ 90 Meal

Chlortetracycline
Type A Medicated Article

CAUTION: Federal law restricts medicated feed
containing this veterinary feed directive (VFD) drug
to use by or on the order of a licensed veterinarian.

See mixing directions, claims, cautions
and warnings on back.

Restricted Drug (California) - Use Only as Directed.
Not for use in humans.
Keep out of reach of children.

Net wt. 50 LB (22.68 Kg)

Pharmgate
ANIMAL HEALTH